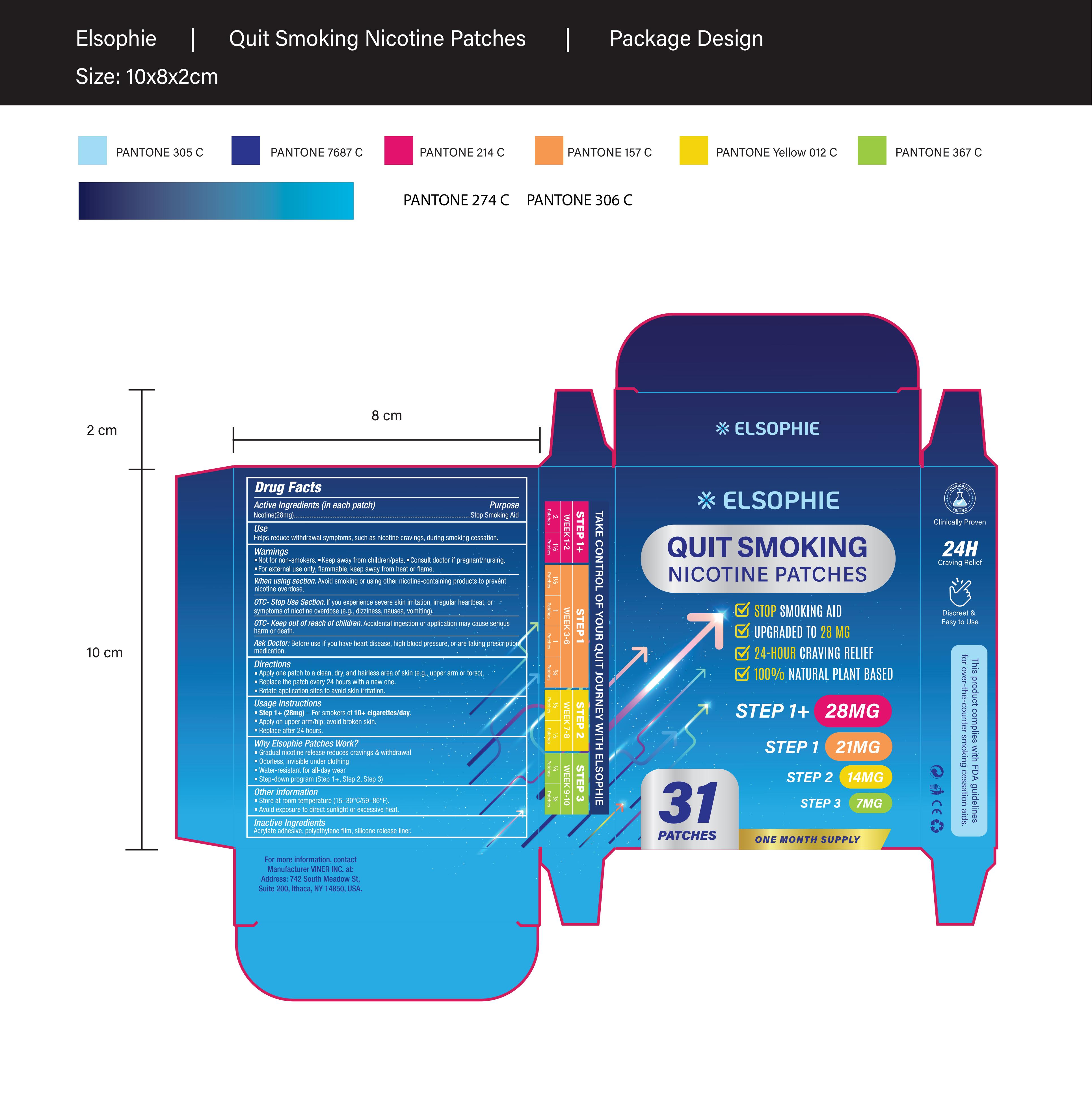 DRUG LABEL: Elsophie Nicotine Patches Quit
NDC: 83818-014 | Form: PATCH
Manufacturer: Shenzhen Xinxin Yunhai Technology Co., Ltd.
Category: otc | Type: HUMAN OTC DRUG LABEL
Date: 20250603

ACTIVE INGREDIENTS: NICOTINE 28 mg/100 1
INACTIVE INGREDIENTS: ARCHANGELENONE; DIETHYLENE GLYCOL ABIETATE; POLYETHYLENE

83818-014

Active Ingredient

Nicotine: 28 mg

Purpose

stop smoking aid

Use

Helps reduce withdrawal symptoms, such as nicotine cravings, during smoking cessation

Warnings

Keep away from children/pets

Do not use

If you are allergic to nicotine or any adhesive patches.

If you are pregnant or breastfeeding, unless directed by a doctor.

When Using

Avoid smoking or using other nicotine-containing products to prevent nicotine overdose.

Stop Use

If you experience severe skin irritation, irregular heartbeat, or symptoms of nicotine overdose (e.g., dizziness, nausea, vomiting).

Ask Doctor

Before use if you have heart disease, high blood pressure, or are taking prescription medication.

Keep Out Of Reach Of Children

Accidental ingestion or application may cause serious harm or death.

Directions

Apply one patch to a clean, dry, and hairless area of skin (e.g., upper arm or torso).
Replace the patch every 24 hours with a new one.
Rotate application sites to avoid skin irritation.

Other information

Store at room temperature (15–30°C/59–86°F).
Avoid exposure to direct sunlight or excessive heat.

Inactive ingredients

Acrylate adhesive, polyethylene film, silicone release liner.

Questions

For more information, contact VINER INC. at:

Address: 742 South Meadow St, Suite 200, Ithaca, NY 14850, USA.